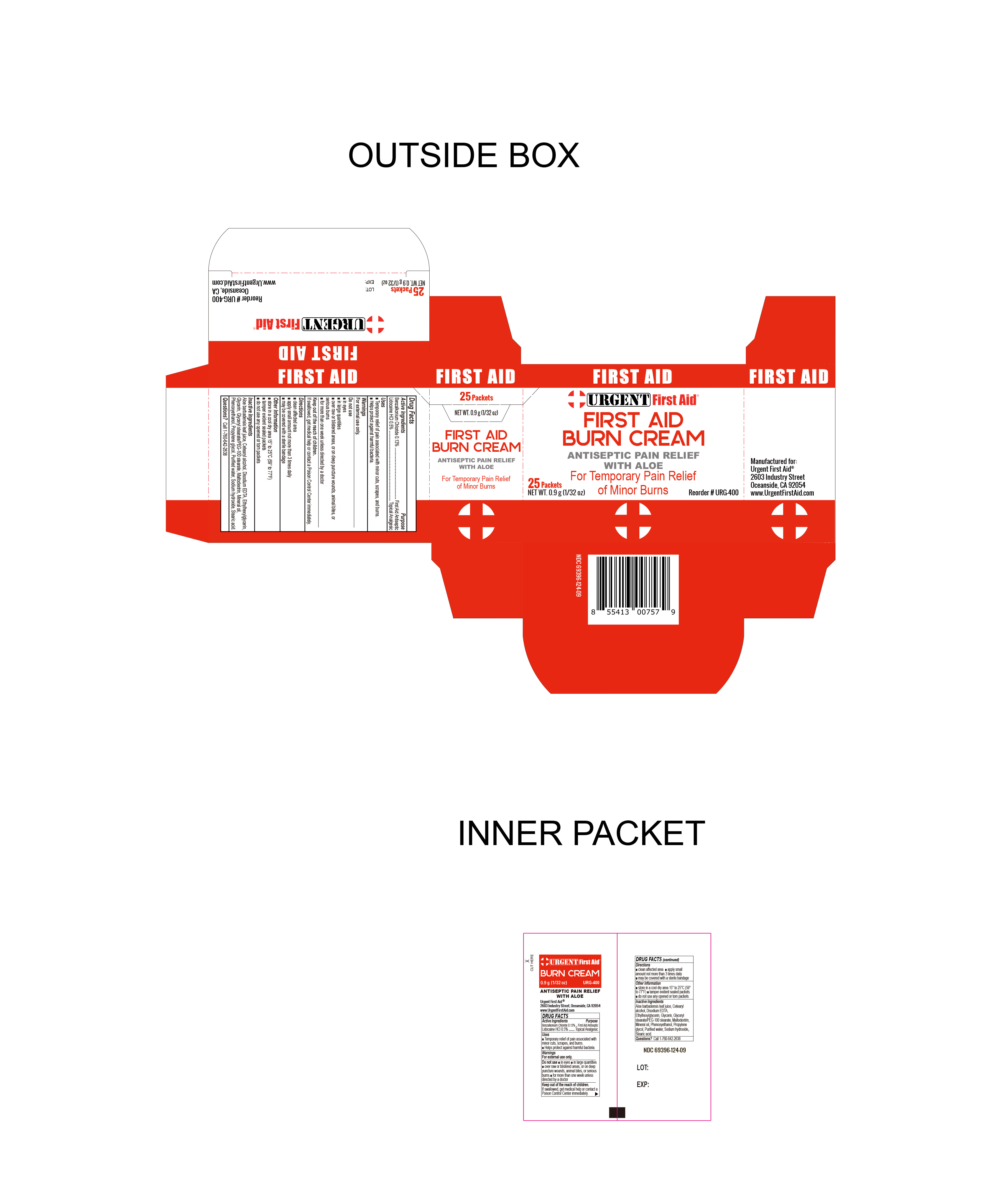 DRUG LABEL: Burn Cream
NDC: 69396-124 | Form: CREAM
Manufacturer: Trifecta Pharmaceuticals USA LLC
Category: otc | Type: HUMAN OTC DRUG LABEL
Date: 20250823

ACTIVE INGREDIENTS: LIDOCAINE HYDROCHLORIDE 0.005 g/1 g; BENZALKONIUM CHLORIDE 0.0013 g/1 g
INACTIVE INGREDIENTS: GLYCERYL STEARATE/PEG-100 STEARATE; WATER; EDETATE DISODIUM; CETOSTEARYL ALCOHOL; ETHYLHEXYLGLYCERIN; PROPYLENE GLYCOL; ALOE VERA LEAF; TROLAMINE; MALTODEXTRIN; MINERAL OIL; PHENOXYETHANOL; STEARIC ACID; GLYCERIN

Urgent First Aid Burn Cream

Active Ingredient

Lidocaine HCI 0.5%

Purpose

Topical Analgesic

ACTIVE INGREDIENT

Benzalkonium Chloride 0.13%

Purpose

First Aid Antiseptic

Uses

Temporary Relief of pain associated with minor cuts, scrapes and burns.

Helps protect against harmful bacteria.

Warnings

For external Use Only

Do not use

- in eyes
- in large quantities
- over raw or blistered areas, or on deep puncture wounds, animal bites, or serious burns
- for more than one week unless directed by a doctor

Directions

- Clean the affected area
- Apply a small amount not more than 3 times daily
- May be covered with a sterile bandage

Inactive Ingredients

Aloe barbadensis leaf juice, Cetearyl alcohol, Disodium EDTA, Ethylhexylglycerin, Glycerin, Glyceryl stearate/PEG-100 stearate, Maltodextrin, Mineral oil, Phenoxyethanol, Propylene glycol, purified water, stearic acid, Triethanolamine.

Questions

To reorder:

Call 1-760-642-2638

Storage Information

- Store in cool dry area 15° to 25°C (59° to 77°F).
- tamper evident sealed packets
- do not use any opened or torn packets

Keep out of reach of children

If swallowed, get medical help or contact a Poison Control Center immediately.

Other Information

Manufactured for:

Urgent First Aid®

2603 Industry Street

Oceanside, CA. 92054 USA

www.UrgentFirstAid.com

Reorder # URG-400